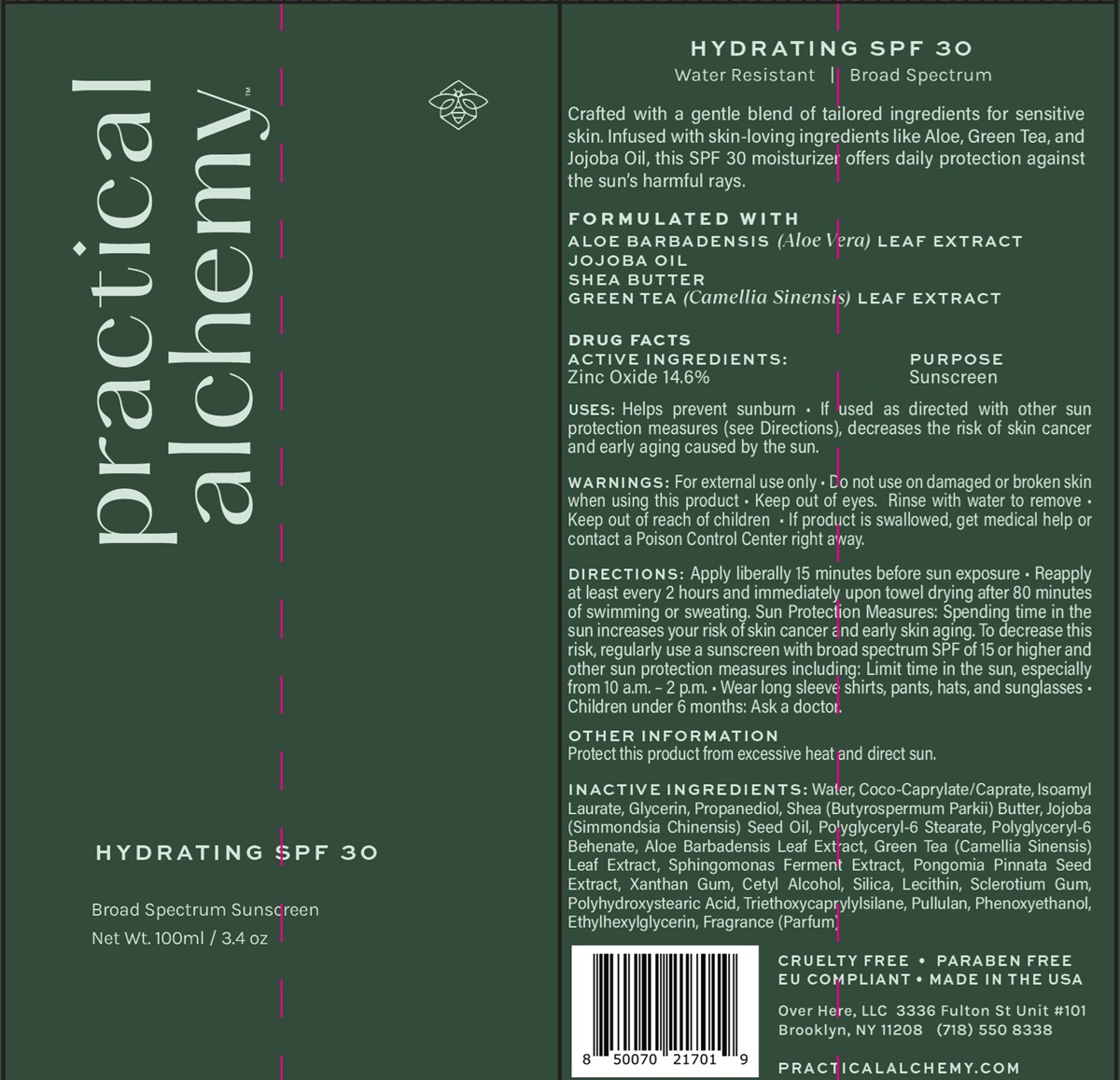 DRUG LABEL: Practical Alchemy Hydrating SPF 30
NDC: 84994-001 | Form: CREAM
Manufacturer: Over Here, LLC
Category: otc | Type: HUMAN OTC DRUG LABEL
Date: 20251112

ACTIVE INGREDIENTS: ZINC OXIDE 14.6 g/100 g
INACTIVE INGREDIENTS: XANTHAN GUM; SILICA; LECITHIN, SOYBEAN; GLYCERIN; PULLULAN; ALOE VERA LEAF; SCLEROTIUM GUM; WATER; POLYGLYCERYL-6 BEHENATE; COCO-CAPRYLATE/CAPRATE; PHENOXYETHANOL; POLYHYDROXYSTEARIC ACID (2300 MW); CETYL ALCOHOL; PROPANEDIOL; ETHYLHEXYLGLYCERIN; SHEA BUTTER; ISOAMYL LAURATE; JOJOBA OIL; GREEN TEA LEAF; TRIETHOXYCAPRYLYLSILANE

Practical Alchemy Hydrating SPF 30

HYDRATING SPF 30

Water Resistant and Broad Spectrum

Crafted with a gentle blend of tailored ingredients for sensitive skin. Infused with skin-loving ingredients like Aloe, Green Tea, and Jojoba Oil, this SPF 30 moisturizer offers daily protection against the sun's harmful rays.

FORMULATED WITH

ALOE BARBADENSIS (Aloe Vera) LEAF EXTRACT

JOJOBA OIL

SHEA BUTTER

GREEN TEA (Camellia Sinensis) LEAF EXTRACT

DRUG FACTS ACTIVE INGREDIENTS:

Zinc Oxide 14.6%

PURPOSE

Sunscreen

USES:

Helps prevent sunburn • If used as directed with other sun protection measures (see Directions), decreases the risk of skin cancer and early aging caused by the sun.

WARNINGS:

For external use only • Do not use on damaged or broken skin when using this product • Keep out of eyes. Rinse with water to remove • Keep out of reach of children • If product is swallowed, get medical help or contact a Poison Control Center right away.

DIRECTIONS:

Apply liberally 15 minutes before sun exposure • Reapply at least every 2 hours and immediately upon towel drying after 80 minutes of swimming or sweating. Sun Protection Measures: Spending time in the sun increases your risk of skin cancer and early skin aging. To decrease this risk, regularly use a sunscreen with broad spectrum SPF of 15 or higher and other sun protection measures including: Limit time in the sun, especially from 10 a.m. - 2 pm • Wear long sleeve shirts, pants, hats, and sunglasses • Children under 6 months: Ask a doctor.

OTHER INFORMATION

Protect this product from excessive heat and direct sun.

INACTIVE INGREDIENTS

Water, Coco-Caprylate/Caprate, Isoamyl Laurate, Glycerin, Propanediol, Shea (Butyrospermum Parkii) Butter, Jojoba (Simmondsia Chinensis) Seed Oil, Polyglyceryl-6 Stearate, Polyglycerl-6 Behenate, Aloe Barbadensis Leaf Extract, Green Tea (Camellia Sinensis) Leaf Extract,Sphingomonas Ferment Extract, Pongomia Pinnata Seed Extract, Xanthan Gum, Cetyl Alcohol, Silica, Lecithin, Sclerotium Gum, Polyhydroxystearic Acid, Triethoxycaprylylsilane, Pullulan, Phenoxyethanol, Ethylhexylglycerin, Fragrance (Parfum)